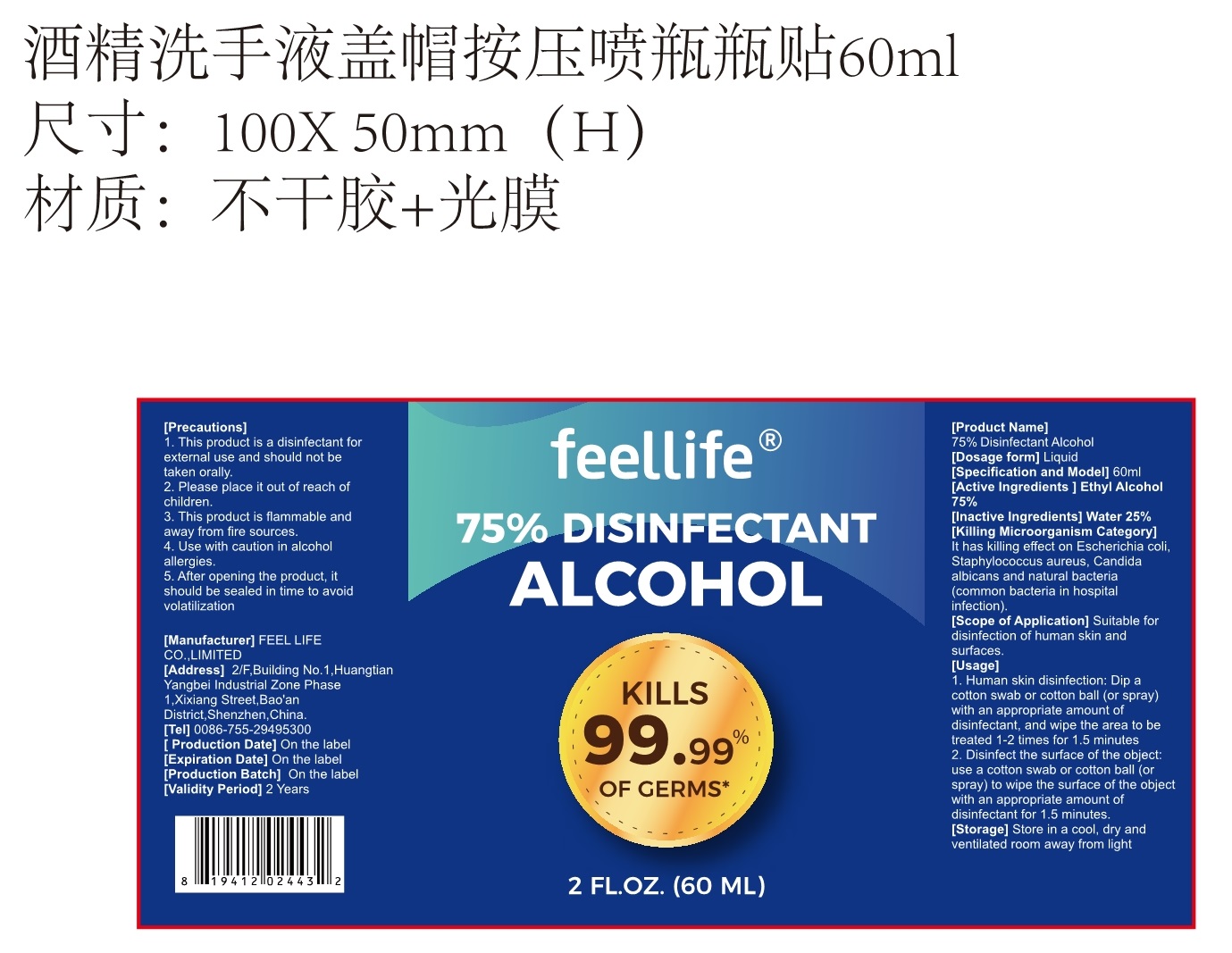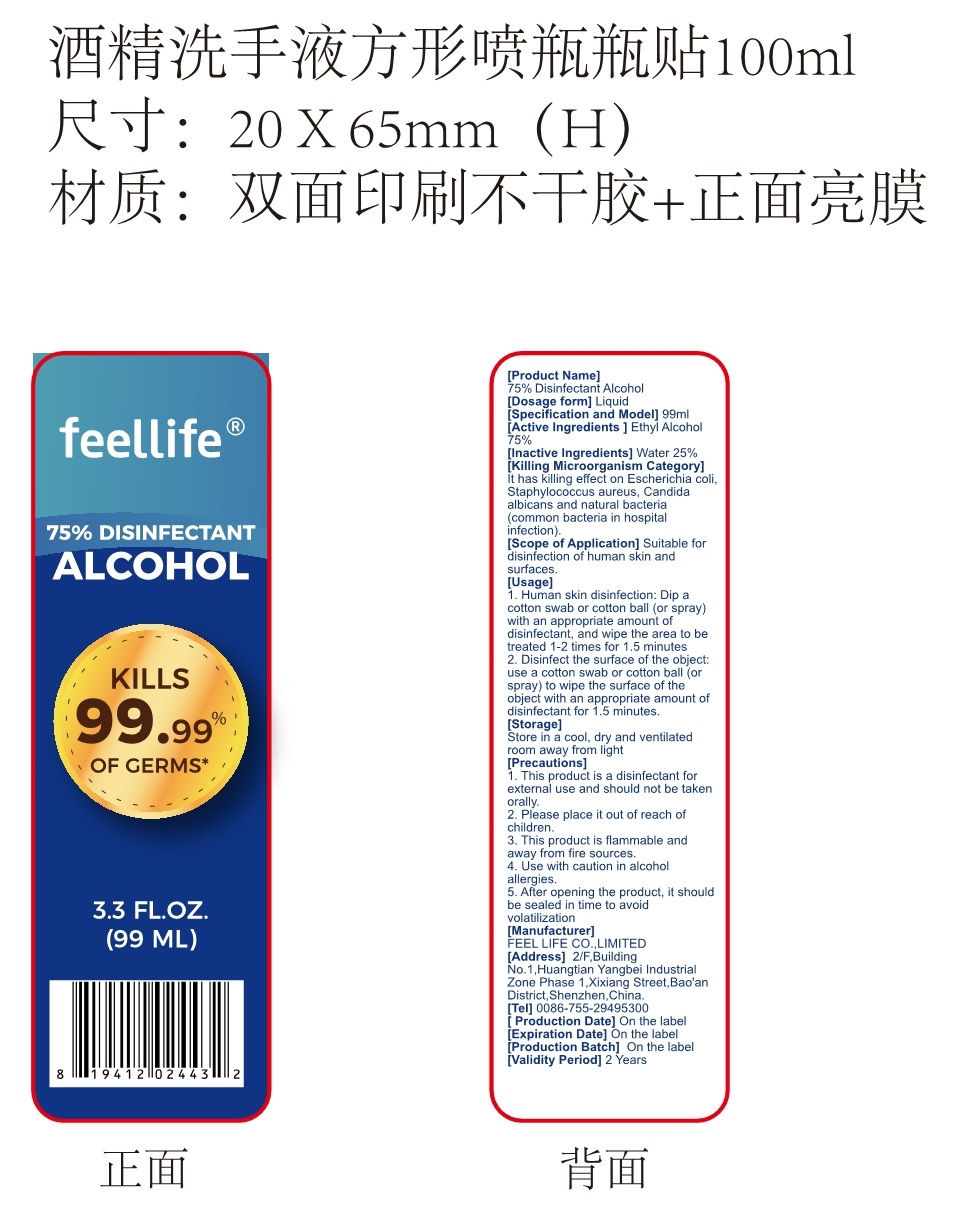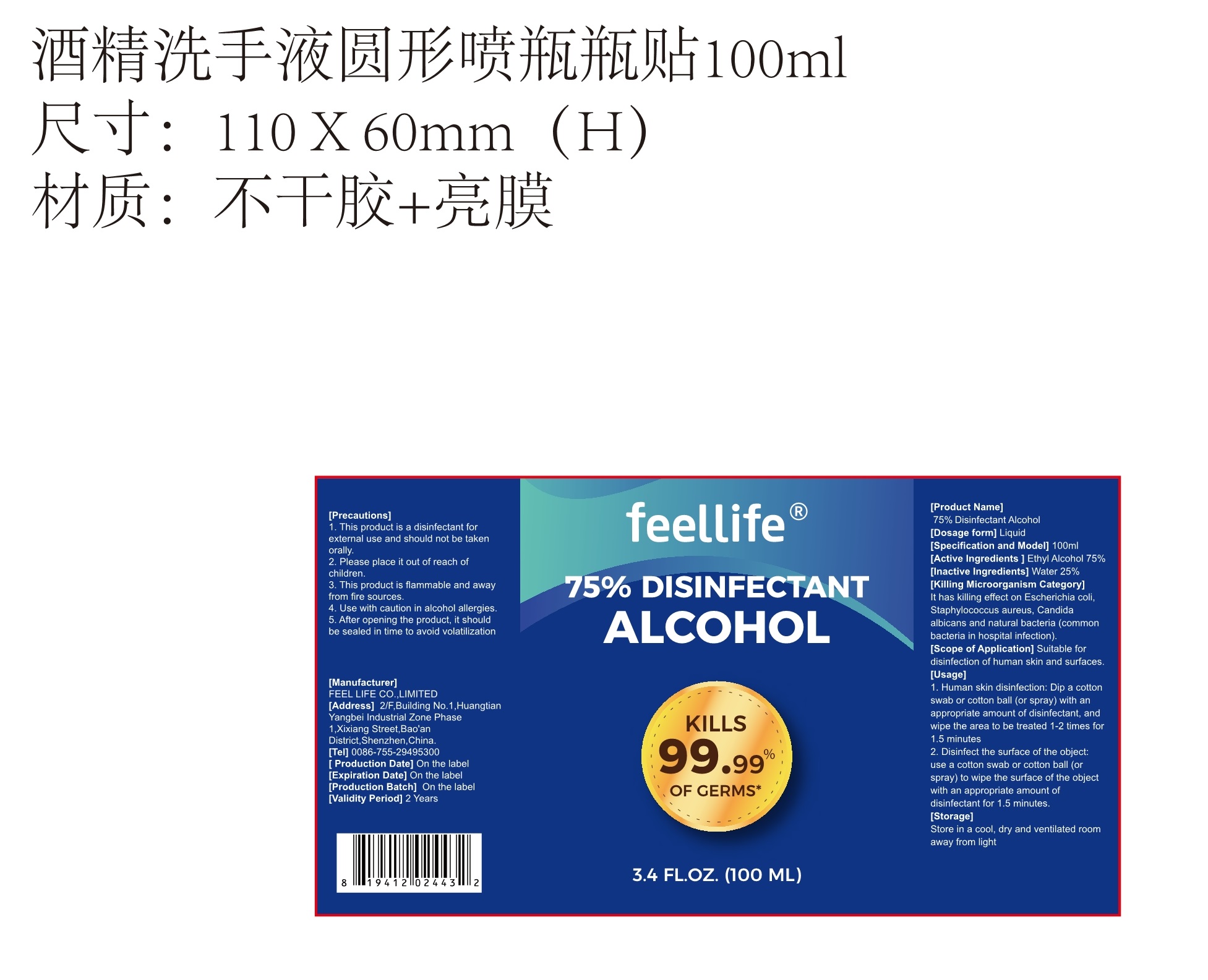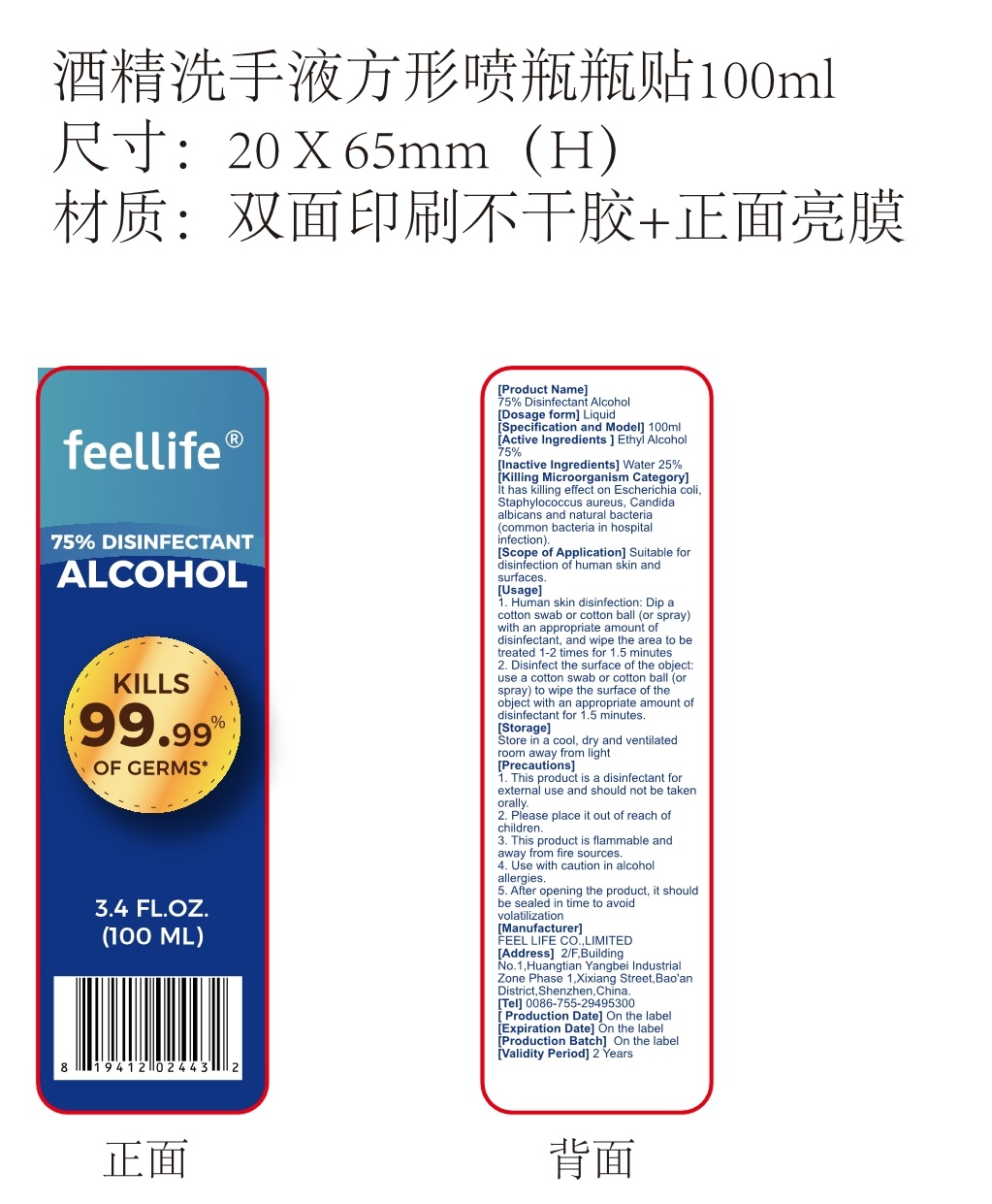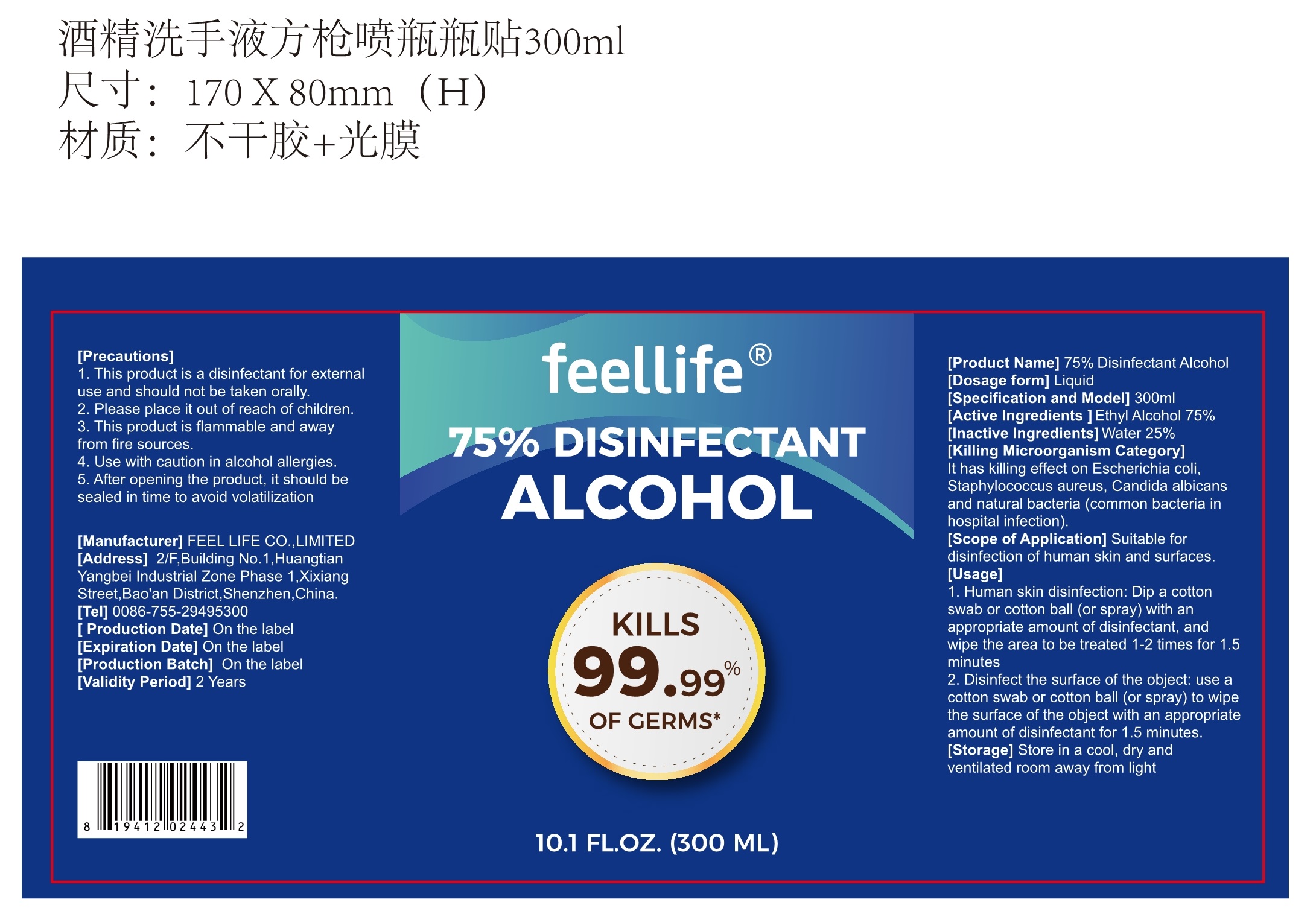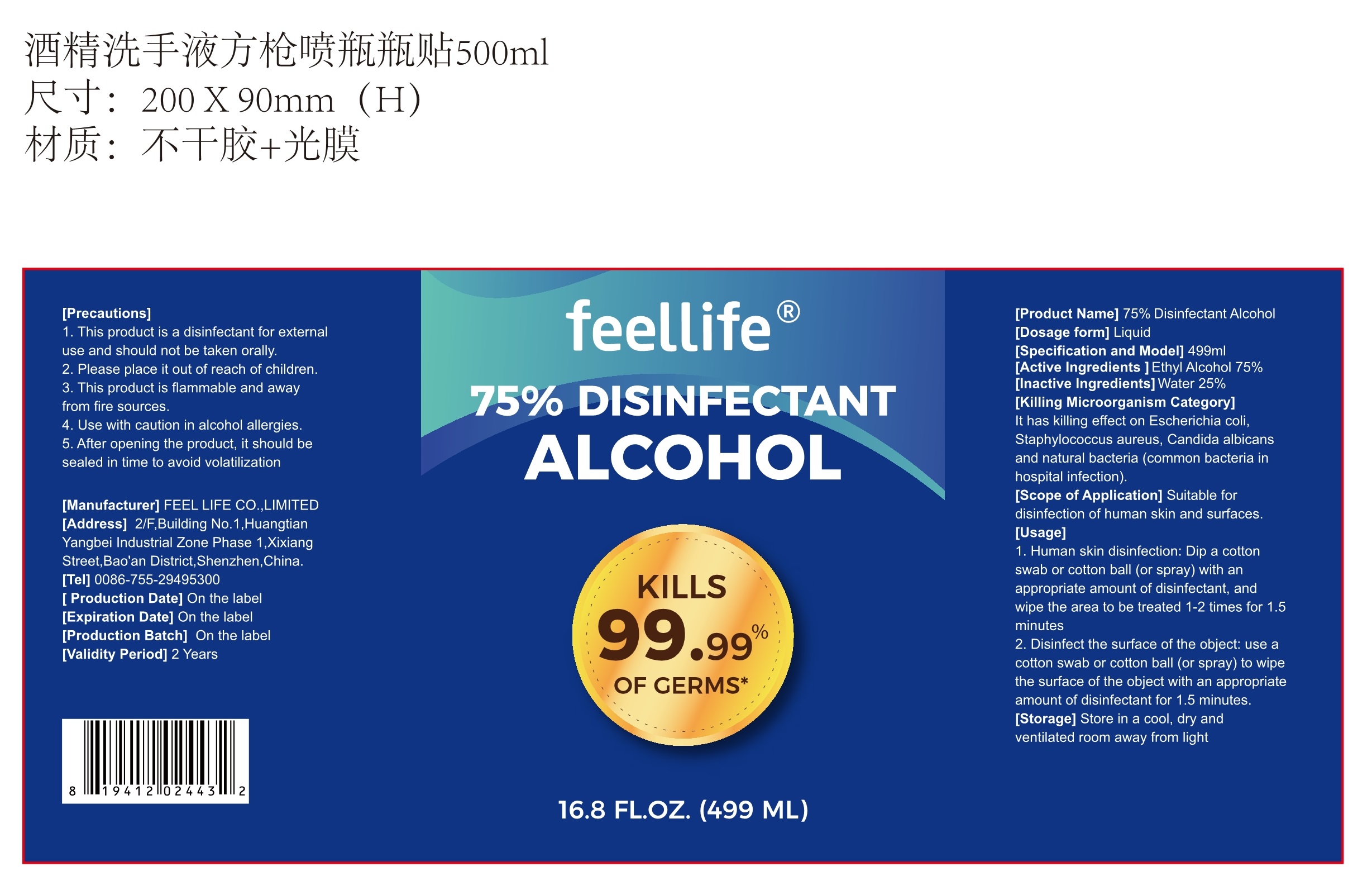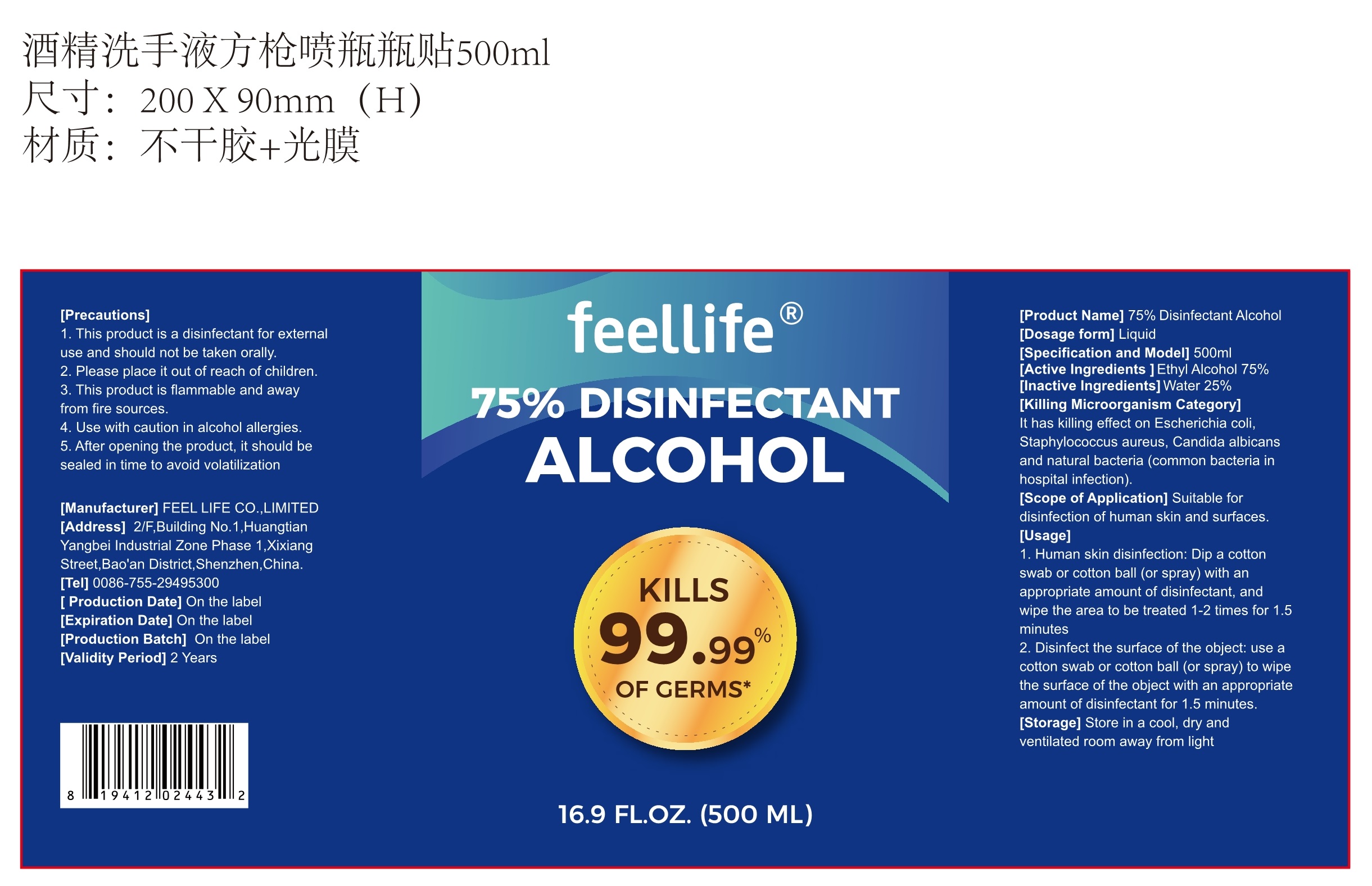 DRUG LABEL: 75%  Disinfectant Alcohol
NDC: 75242-008 | Form: LIQUID
Manufacturer: CANNAPRESSO HEALTH. INC
Category: otc | Type: HUMAN OTC DRUG LABEL
Date: 20200820

ACTIVE INGREDIENTS: ALCOHOL 75 mL/100 mL
INACTIVE INGREDIENTS: WATER

75242-008
75% Disinfectant Alcohol

Active Ingredient(s)

Ethyl Alcohol 75%

Purpose

It has killing effect on Escherichia coli, Staphylococcus aureus, Candida albicans and natural bacteria (common bacteria in hospital infection).

Use

1. Human skin disinfection: Dip a cotton swab or cotton ball (or spray) with an appropriate amount of disinfectant, and wipe the area to be treated 1-2 times for 1.5 minutes
2. Disinfect the surface of the object: use a cotton swab or cotton ball (or spray) to wipe the surface of the object with an appropriate amount of disinfectant for 1.5 minutes.

Warnings

1. This product is a disinfectant for external use and should not be taken orally.
2. Please place it out of reach of children.
3. This product is flammable and away from fire sources.
4. Use with caution in alcohol allergies.
5. After opening the product, it should be sealed in time to avoid volatilization

Do not use

/

WHEN USING

/

STOP USE

/

KEEP OUT OF REACH OF CHILDREN

/

Directions

1. This product is a disinfectant for external use and should not be taken orally.
2. Please place it out of reach of children.
3. This product is flammable and away from fire sources.
4. Use with caution in alcohol allergies.
5. After opening the product, it should be sealed in time to avoid volatilization

Inactive ingredients

Water 25%